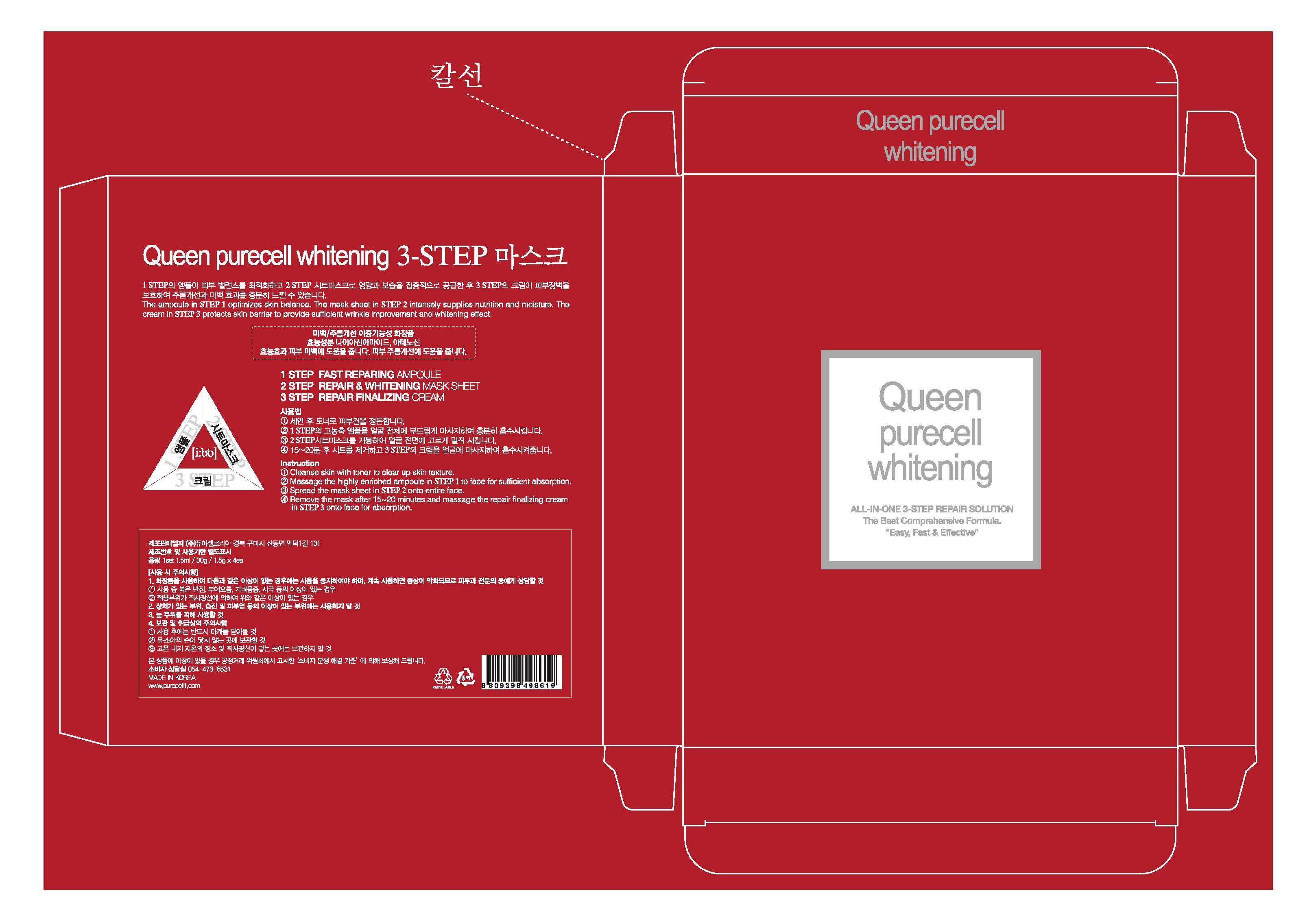 DRUG LABEL: QUEEN PURECELL WHITENING 3-STEP MASK
NDC: 71609-0005 | Form: KIT | Route: TOPICAL
Manufacturer: Purecell Korea Co., Ltd.
Category: otc | Type: HUMAN OTC DRUG LABEL
Date: 20170807

ACTIVE INGREDIENTS: NIACINAMIDE 2 g/100 mL; ADENOSINE 0.04 g/100 mL; NIACINAMIDE 2 g/100 g; ADENOSINE 0.04 g/100 g; NIACINAMIDE 2 g/100 g; ADENOSINE 0.04 g/100 g
INACTIVE INGREDIENTS: WATER; WATER; WATER

Drug Facts

ACTIVE INGREDIENT

NIACINAMIDE, ADENOSINE

INACTIVE INGREDIENT

Water, Butylene Glycol, Glycerin, Sodium Hyaluronate, Allantoin, etc.

PURPOSE

WHITENING & ANTI-WRINKLE

keep out of reach of the children

INDICATIONS AND USAGE

1. Cleanse skin with toner to clear up skin texture.
2. Massage the highly enriched ampoule in STEP 1 to face for sufficient absorption.
3. Spread the mask sheet in STEP 2 onto entire face.
4. Remove the mask after 15-20 minutes and massage the repair finalizing cream in STEP 3 onto face for absorption.

WARNINGS

1. If the following symptoms occur after product use, stop using the product immediately and consult a dermatologist (continuous use can exacerbate the symptoms).
1) Occurrence of red spots, swelling, itchiness, and other skin irritation
2) If the symptoms above occur after the application area is exposed to direct sunlight
2. Do not use on open wounds, eczema, and other skin irritations
3. Precaution for Storage and Handling
1) Close the lid after use
2) Keep out of reach of infants and children
3) Do not to store in a place with high/low temperature and exposed to direct sunlight

4. Use as avoiding eye areas.

DOSAGE AND ADMINISTRATION

for external use only